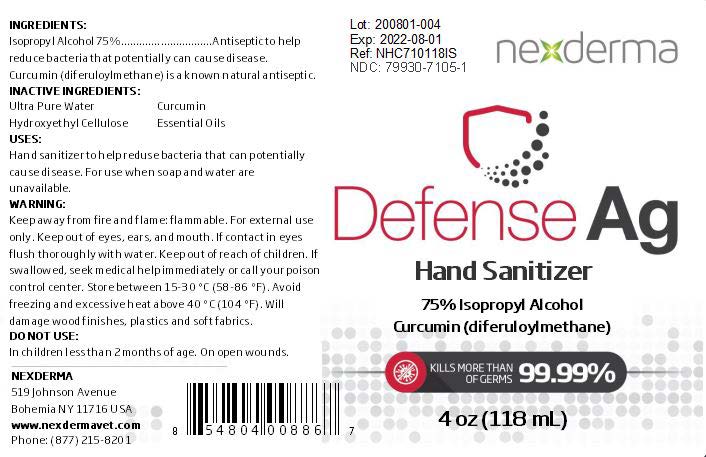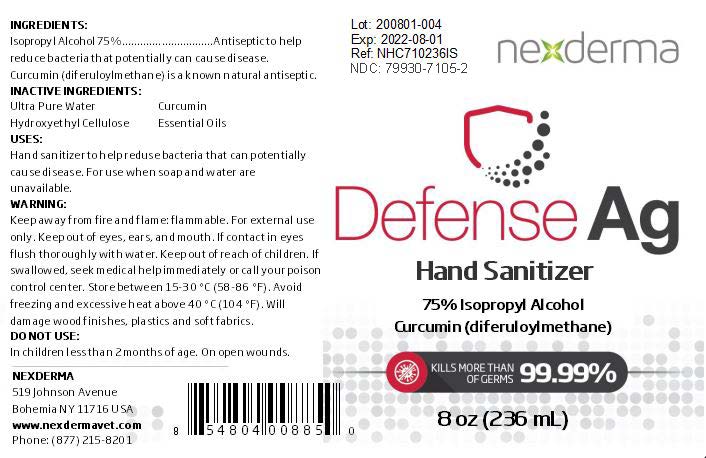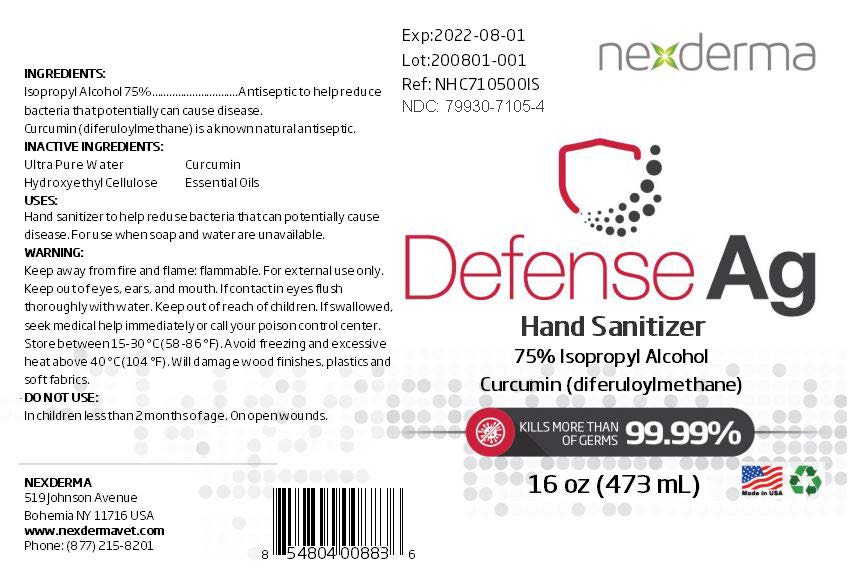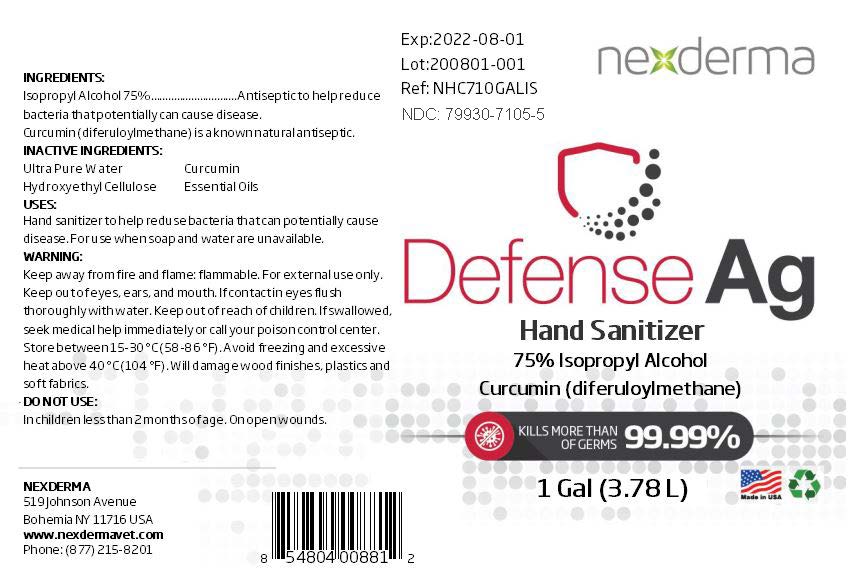 DRUG LABEL: Defense AG Hand Sanitizer
NDC: 79930-7105 | Form: GEL
Manufacturer: Nexderma
Category: otc | Type: HUMAN OTC DRUG LABEL
Date: 20200925

ACTIVE INGREDIENTS: ISOPROPYL ALCOHOL 75 mL/100 mL
INACTIVE INGREDIENTS: HYDROXYETHYL CELLULOSE, UNSPECIFIED 0.2 mL/100 mL; CURCUMIN 1.3 mL/100 mL; WATER

IPA Hand Sanitizer DAG-revised

Active Ingredient(s)

Isopropyl Alcohol 75% v/v. Antiseptic to help reduce bacteria that potentially can cause disease

Inactive ingredients

Ultra Pure Water, Hydroxyethyl Cellulose, Curcumin

Purpose

To help reduce bacteria that potentially can cause disease. For use when soap and water are not available.

Use

Hand Sanitizer to help reduce bacteria that potentially can cause disease. For use when soap and water are unavailable.

Warnings

Keep away form fire and flame.
Flammable
For external use on hands only.
Keep out of eye, ears and mouth.
If contact in eyes, flush thoroughly with water.
Keep out of reach of children.
If swallowed seek medical help immediately or call your poison control center.
Store between 15-30 (58-86F)
Avoid freezing and excessive heat above 40C (104F)
Will damage wood finishes, plastics and some fabrics.

Do not use

- in children less than 2 months of age
- on open skin wounds

KEEP OUT OF REACH OF CHILDREN

Adult supervision recommended for children under 6 years old.

Directions

Dosage: Place enough product on hands to cover all surfaces. Rub hands together until dry.

Administration: Topical

Other information

- Store between 15-30C (59-86F)
- Avoid freezing and excessive heat above 40C (104F)